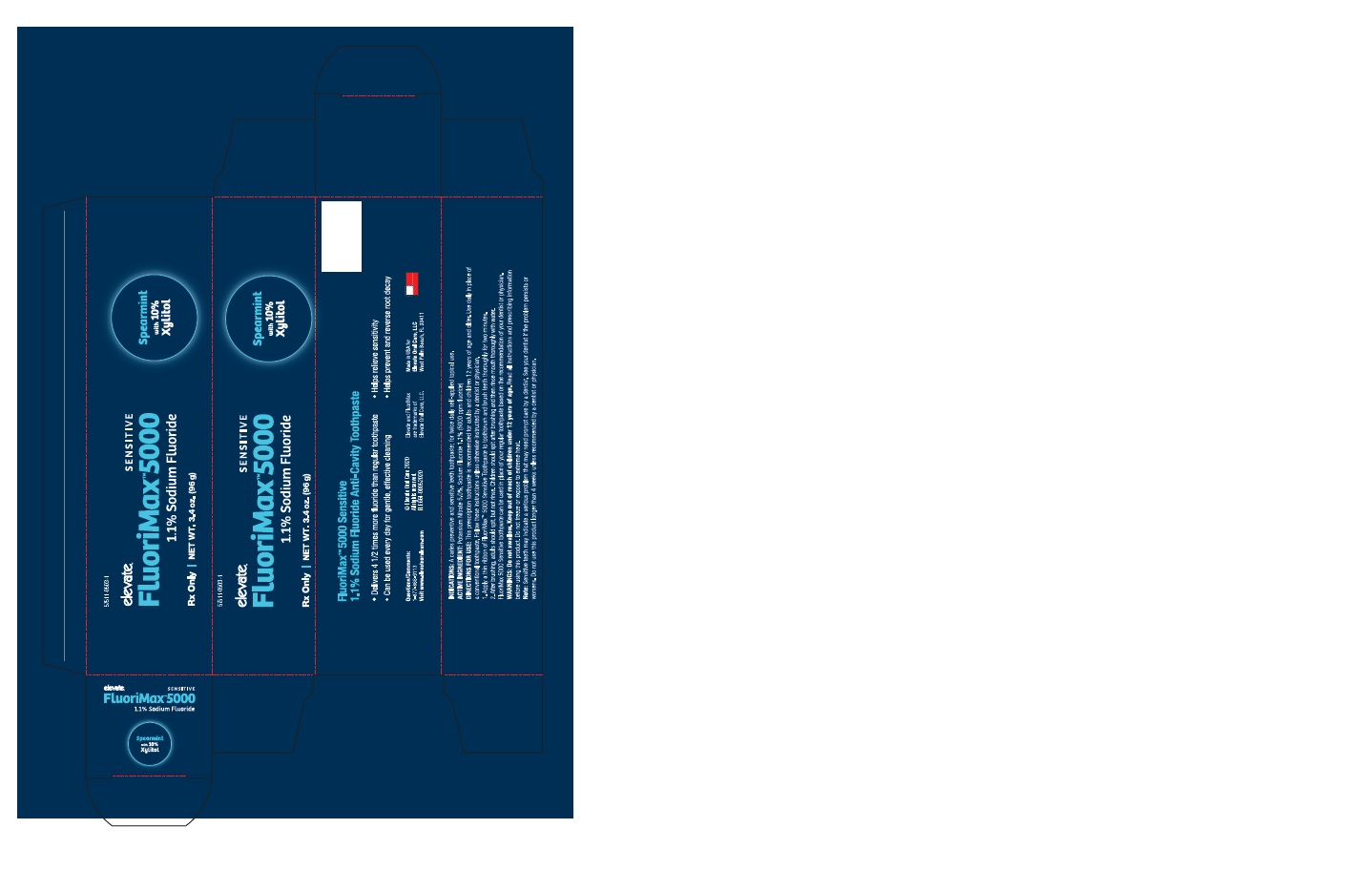 DRUG LABEL: FluoriMax 5000 Sensitive
NDC: 57511-0503 | Form: PASTE, DENTIFRICE
Manufacturer: Elevate Oral Care
Category: prescription | Type: HUMAN PRESCRIPTION DRUG LABEL
Date: 20200831

ACTIVE INGREDIENTS: POTASSIUM NITRATE 5 g/100 g; SODIUM FLUORIDE 1.1 g/100 g

FluoriMax 5000 1.1% Sodium Fluoride & 5% Potassium Nitrate Toothpaste

Warnings Section

Do not swallow. Keep out of reach of children under 12 years of age. Read all the instructions and prescribing information before using this product. Do not freeze or expose to extreme heat